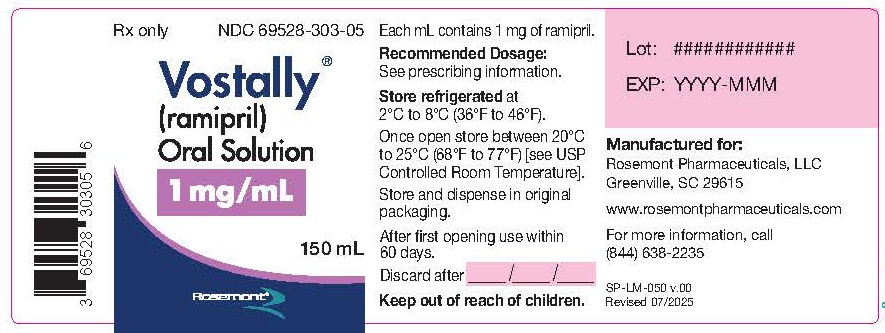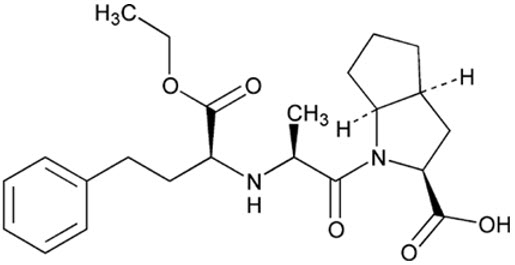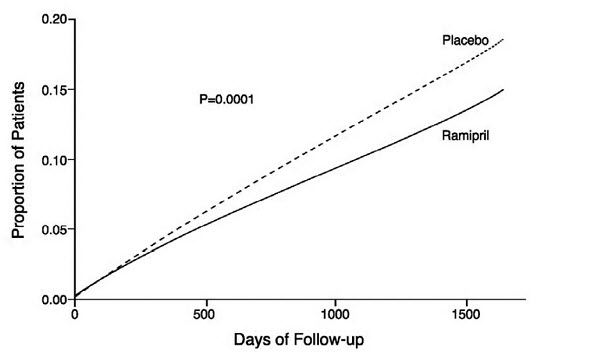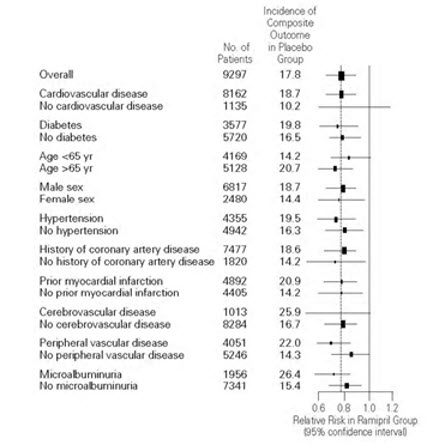 DRUG LABEL: Vostally
NDC: 69528-303 | Form: SOLUTION
Manufacturer: Metacel Pharmaceuticals, LLC
Category: prescription | Type: HUMAN PRESCRIPTION DRUG LABEL
Date: 20250815

ACTIVE INGREDIENTS: RAMIPRIL 1 mg/1 mL
INACTIVE INGREDIENTS: METHYLPARABEN 1.8 mg/1 mL; ETHYLPARABEN; SUCRALOSE; CITRIC ACID MONOHYDRATE; PEPPERMINT; WATER

HIGHLIGHTS OF PRESCRIBING INFORMATION

These highlights do not include all the information needed to use VOSTALLY® safely and effectively. See full prescribing information for VOSTALLY.
VOSTALLY (ramipril) oral solution
Initial U.S. Approval: 1991

WARNING: FETAL TOXICITY

See full prescribing information for complete boxed warning

- When pregnancy is detected, discontinue VOSTALLY as soon as possible (5.1).
- Drugs that act directly on the renin-angiotensin system can cause injury and death to the developing fetus (5.1).

1 INDICATIONS AND USAGE

VOSTALLY is an angiotensin converting enzyme (ACE) inhibitor indicated:

- for the treatment of hypertension in adults, to lower blood pressure. Lowering blood pressure reduces the risk of fatal and nonfatal cardiovascular events, primarily strokes and myocardial infarctions (1.1).
- In patients 55 years or older at high risk of developing a major cardiovascular event, VOSTALLY is indicated to reduce the risk of myocardial infarction, stroke, or death from cardiovascular causes (1.2).
- In adult patients with post-myocardial infarction heart failure to reduce the risk of cardiovascular death and hospitalization for heart failure (1.3).

2 DOSAGE AND ADMINISTRATION

- Hypertension: Initial dose is 2.5 mg to 20 mg orally once daily. Adjust dosage according to blood pressure response after 2–4 weeks of treatment. The usual maintenance dose following titration is 2.5 mg to 20 mg orally daily as a single dose or equally divided doses (2.2).
- Reduction in the risk of myocardial infarction, stroke, or death from cardiovascular causes: 2.5 mg orally once daily for 1 week, 5 mg orally once daily for 3 weeks, and increased as tolerated to a maintenance dose of 10 mg orally once daily (2.3).
- Heart failure post-myocardial infarction: Starting dose of 2.5 mg orally twice daily. If patient becomes hypotensive at this dose, decrease dosage to 1.25 mg orally twice daily. Titrate at 3-week intervals as tolerated to a target dose of 5 mg orally twice daily (2.4).

3 DOSAGE FORMS AND STRENGTHS

Oral Solution: 1 mg/mL

4 CONTRAINDICATIONS

- Angioedema or hypersensitivity related to previous treatment with an ACE inhibitor, or a history of hereditary or idiopathic angioedema (4).
- VOSTALLY is contraindicated in combination with a neprilysin inhibitor (e.g., sacubitril). Do not administer VOSTALLY within 36 hours of switching to or from sacubitril/valsartan, a neprilysin inhibitor (4).
- Do not co-administer aliskiren with VOSTALLY in patients with diabetes (4).

5 WARNINGS AND PRECAUTIONS

- Angioedema, increased risk in patients with a prior history (5.2)
- Hypotension (5.3)
- Rare cholestatic jaundice and hepatic failure (5.4)
- Renal impairment: monitor renal function during therapy (5.5)
- Hyperkalemia (5.6)

6 ADVERSE REACTIONS

The most common adverse reactions included cough and hypotension (6.1).

To report SUSPECTED ADVERSE REACTIONS, contact Rosemont Pharmaceuticals, LLC at 1-844-638-2235 or FDA at 1-800-FDA-1088 or www.fda.gov/medwatch

7 DRUG INTERACTIONS

- Diuretics: Excessive drop in blood pressure (7.1).
- Potassium-sparing diuretics/potassium supplements: Hyperkalemia (7.2)
- Dual inhibition of the renin-angiotensin system: Increased risk of renal impairment, hypotension, and hyperkalemia (7.3)
- Lithium: Increase serum lithium levels, symptoms of lithium toxicity (7.4).
- Gold: Nitritoid reactions have been reported (7.5).
- NSAID use may lead to increased risk of renal impairment and loss of antihypertensive effect (7.6).
- mTOR inhibitor or neprilysin inhibitor use may increase angioedema risk (7.7).

8 USE IN SPECIFIC POPULATIONS

- Lactation: Advise not to breastfeed. (8.2)

FULL PRESCRIBING INFORMATION

WARNING: FETAL TOXICITY

- When pregnancy is detected, discontinue VOSTALLY as soon as possible [see Warnings and Precautions (5.1)] .
- Drugs that act directly on the renin-angiotensin system can cause injury and death to the developing fetus [see Warnings and Precautions (5.1)] .

1 INDICATIONS AND USAGE

1.1 Hypertension

VOSTALLY is indicated for the treatment of hypertension, to lower blood pressure. Lowering blood pressure reduces the risk of fatal and nonfatal cardiovascular events, primarily strokes and myocardial infarctions. These benefits have been seen in controlled trials of antihypertensive drugs from a wide variety of pharmacologic classes including this drug.

Control of high blood pressure should be part of comprehensive cardiovascular risk management, including, as appropriate, lipid control, diabetes management, antithrombotic therapy, smoking cessation, exercise, and limited sodium intake. Many patients will require more than one drug to achieve blood pressure goals. For specific advice on goals and management, see published guidelines, such as those of the National High Blood Pressure Education Program's Joint National Committee on Prevention, Detection, Evaluation, and Treatment of High Blood Pressure (JNC).

Numerous antihypertensive drugs, from a variety of pharmacologic classes and with different mechanisms of action, have been shown in randomized controlled trials to reduce cardiovascular morbidity and mortality, and it can be concluded that it is blood pressure reduction, and not some other pharmacologic property of the drugs, that is largely responsible for those benefits. The largest and most consistent cardiovascular outcome benefit has been a reduction in the risk of stroke, but reductions in myocardial infarction and cardiovascular mortality also have been seen regularly.

Elevated systolic or diastolic pressure causes increased cardiovascular risk, and the absolute risk increase per mmHg is greater at higher blood pressures, so that even modest reductions of severe hypertension can provide substantial benefit. Relative risk reduction from blood pressure reduction is similar across populations with varying absolute risk, so the absolute benefit is greater in patients who are at higher risk independent of their hypertension (for example, patients with diabetes or hyperlipidemia), and such patients would be expected to benefit from more aggressive treatment to a lower blood pressure goal.

Some antihypertensive drugs have smaller blood pressure effects (as monotherapy) in black patients, and many antihypertensive drugs have additional approved indications and effects (e.g., on angina, heart failure, or diabetic kidney disease). These considerations may guide selection of therapy.

VOSTALLY may be used alone or in combination with thiazide diuretics.

1.2 Reduction in the Risk of Myocardial Infarction, Stroke, and Death from Cardiovascular Causes

VOSTALLY is indicated in patients 55 years or older at high risk of developing a major cardiovascular event because of a history of coronary artery disease, stroke, peripheral vascular disease, or diabetes that is accompanied by at least one other cardiovascular risk factor (hypertension, elevated total cholesterol levels, low HDL levels, cigarette smoking, or documented microalbuminuria), to reduce the risk of myocardial infarction, stroke, or death from cardiovascular causes.

1.3 Post-Myocardial Infarction Heart Failure

VOSTALLY is indicated in adult patients with post-myocardial infarction heart failure to reduce the risk of cardiovascular death and hospitalization for heart failure [see Clinical Studies (14.3)] .

2 DOSAGE AND ADMINISTRATION

2.1 Important Administration Information

Instruct patients or caregivers to use an oral dosing syringe or oral dosing cup to correctly measure the prescribed amount of medication. Inform patients that oral dosing syringes may be obtained from their pharmacy.

2.2 Recommended Dosage in Hypertension

The recommended initial dose for patients not receiving a diuretic is 2.5 mg orally once a day. Adjust dose according to blood pressure response. The usual maintenance dosage range is 2.5 mg to 20 mg orally per day administered as a single dose or in two equally divided doses. In some patients treated once daily, the antihypertensive effect may diminish toward the end of the dosing interval. In such patients, consider an increase in dosage or twice daily administration.

2.3 Recommended Dosage in Reduction in Risk of Myocardial Infarction, Stroke, and Death from Cardiovascular Causes

Initiate dosing at 2.5 mg orally once daily for 1 week, 5 mg orally once daily for the next 3 weeks, and then increase as tolerated, to a maintenance dose of 10 mg orally once daily. If the patient is hypertensive or recently post-myocardial infarction, VOSTALLY can also be given as a divided dose.

2.4 Recommended Dosage in Post-Myocardial Infarction Heart Failure

For the treatment of patients with post-myocardial infarction heart failure, the recommended starting dose of VOSTALLY is 2.5 mg orally twice daily (5 mg orally per day). A patient who becomes hypotensive at this dose may be switched to 1.25 mg orally twice daily. After one week at the starting dose, increase dose (if tolerated) toward a target dose of 5 mg orally twice daily, with dosage increases being about 3 weeks apart.

After the initial dose of VOSTALLY, observe the patient under medical supervision for at least two hours and until blood pressure has stabilized for at least an additional hour. If possible, reduce the dose of any concomitant diuretic as this may diminish the likelihood of hypotension. The appearance of hypotension after the initial dose of VOSTALLY does not preclude subsequent careful dose titration with the drug, following effective management of the hypotension [see Warnings and Precautions (5.5), Drug Interactions (7.1)] .

2.5 Dosage Adjustments

Renal Impairment

Establish baseline renal function in patients initiating VOSTALLY. In patients with creatinine clearance ≤40 mL/min, 25% of the usual dose of ramipril is expected to produce full therapeutic levels of ramiprilat [see Use in Specific Populations (8.6)] .

Hypertension

For patients with hypertension and renal impairment, the recommended initial dosage of VOSTALLY is 1.25 mg orally once daily. Dosage may be titrated upward until blood pressure is controlled or to a maximum total daily dose of 5 mg orally.

Heart Failure Post-Myocardial Infarction

For patients with heart failure and renal impairment, the recommended initial dosage of VOSTALLY is 1.25 mg orally once daily. The dose may be increased to 1.25 mg orally twice daily, and up to a maximum dose of 2.5 mg orally twice daily depending on clinical response and tolerability.

Volume Depletion or Renal Artery Stenosis

Blood pressure decreases associated with any dose of VOSTALLY depend, in part, on the presence or absence of volume depletion (e.g., past and current diuretic use) or the presence or absence of renal artery stenosis. If such circumstances are suspected to be present, initiate dosing at 1.25 mg orally once daily. Adjust dosage according to blood pressure response.

3 DOSAGE FORMS AND STRENGTHS

VOSTALLY (ramipril) oral solution 1 mg/mL is a clear, colorless solution. It is available in a 150 mL volume.

4 CONTRAINDICATIONS

VOSTALLY is contraindicated in patients with:

- a history of angioedema or hypersensitivity to this product or any other ACE inhibitor [see Warnings and Precautions (5.2)]
- hereditary or idiopathic angioedema [see Warnings and Precautions (5.2)]

VOSTALLY is contraindicated in combination with a neprilysin inhibitor (e.g., sacubitril). Do not administer VOSTALLY within 36 hours of switching to or from sacubitril/valsartan, a neprilysin inhibitor [see Drug Interactions (7.3)]

Do not co-administer VOSTALLY with aliskiren in patients with diabetes [see Drug Interactions (7.3)]

5 WARNINGS AND PRECAUTIONS

5.1 Fetal Toxicity

VOSTALLY can cause fetal harm when administered to a pregnant woman. Use of drugs that act on the renin-angiotensin system during the second and third trimesters of pregnancy reduces fetal renal function and increases fetal and neonatal morbidity and death. Resulting oligohydramnios can be associated with fetal lung hypoplasia and skeletal deformations. Potential neonatal adverse effects include skull hypoplasia, anuria, hypotension, renal failure, and death. When pregnancy is detected, discontinue VOSTALLY as soon as possible [see Use in Specific Populations (8.1)].

5.2 Angioedema and Anaphylactoid Reactions

Angioedema

Head and Neck Angioedema

Angioedema of the face, extremities, lips, tongue, glottis, and/or larynx, including airway obstruction and some fatal reactions, have occurred in patients treated with ACE inhibitors at any time during treatment. VOSTALLY should be promptly discontinued, and appropriate therapy and monitoring should be provided until complete and sustained resolution of signs and symptoms of angioedema has occurred.

Patients with a history of angioedema unrelated to ACE inhibitor therapy may be at increased risk of angioedema while receiving an ACE inhibitor [see Contraindications (4)]. ACE inhibitors have been associated with a higher rate of angioedema in Black than in non-Black patients. Patients taking concomitant mammalian target of rapamycin (mTOR) inhibitor (e.g., temsirolimus, sirolimus, everolimus) therapy or a neprilysin inhibitor may be at increased risk for angioedema. [see Drug Interactions (7.7)]

Intestinal Angioedema

Intestinal angioedema has been reported in patients treated with ACE inhibitors.

These patients presented with abdominal pain (with or without nausea or vomiting); in some cases, there was no prior history of facial angioedema and C-1 esterase levels were normal. The angioedema was diagnosed by procedures including abdominal CT scan or ultrasound, or at surgery, and symptoms resolved after stopping the ACE inhibitor. Include intestinal angioedema in the differential diagnosis of patients on ACE inhibitors presenting with abdominal pain.

Anaphylactoid Reactions

Anaphylactoid Reactions During Desensitization

Two patients undergoing desensitizing treatment with hymenoptera venom while receiving ACE inhibitors sustained life- threatening anaphylactoid reactions. In the same patients, these reactions were avoided when ACE inhibitors were temporarily withheld, but they reappeared upon inadvertent rechallenge.

Anaphylactoid Reactions During Dialysis

Anaphylactoid reactions have been reported in patients dialyzed with high-flux membranes and treated concomitantly with an ACE inhibitor. In such patients, dialysis must be stopped immediately, and aggressive therapy for anaphylactoid reactions must be initiated. Symptoms have not been relieved by antihistamines in these situations. In these patients, consideration should be given to using a different type of dialysis membrane or a different class of antihypertensive agent. Anaphylactoid reactions have also been reported in patients undergoing low-density lipoprotein apheresis with dextran sulfate absorption.

5.3 Hypotension

General Considerations

VOSTALLY can cause symptomatic hypotension, after the initial dose or when the dosage has been increased. Patients at risk of symptomatic hypotension include those with volume and/or salt depletion of any etiology (e.g., high dose diuretic therapy, dietary salt restriction, renal dialysis, diarrhea, or vomiting). Correct volume and/or salt depletion before initiating therapy with VOSTALLY and monitor for the first two weeks of treatment and whenever the dose of VOSTALLY and/or diuretic is increased.

If excessive hypotension occurs, place the patient in a supine position and, if necessary, treat with intravenous infusion of physiological saline. VOSTALLY treatment usually can be continued following restoration of blood pressure and volume.

Heart Failure Post-Myocardial Infarction

In patients with heart failure post-myocardial infarction who are currently being treated with a diuretic, symptomatic hypotension occasionally can occur following the initial dose of VOSTALLY. If the initial dose of 2.5 mg VOSTALLY cannot be tolerated, use an initial dose of 1.25 mg VOSTALLY to avoid excessive hypotension. Consider reducing the dose of concomitant diuretic to decrease the incidence of hypotension.

Congestive Heart Failure

In patients with congestive heart failure, with or without associated renal insufficiency, VOSTALLY may cause excessive hypotension, which may be associated with oliguria or azotemia and rarely, with acute renal failure and death. In such patients, initiate VOSTALLY therapy under close medical supervision and monitor for the first 2 weeks of treatment and whenever the dose of VOSTALLY or diuretic is increased.

Surgery and Anesthesia

In patients undergoing surgery or during anesthesia with agents that produce hypotension, VOSTALLY may block angiotensin II secondary to compensatory renin release. Hypotension that occurs as a result of this mechanism can be corrected by volume expansion.

5.4 Hepatic Failure

ACE inhibitors, including VOSTALLY, have been associated with a syndrome that starts with cholestatic jaundice and progresses to fulminant hepatic necrosis and sometimes death. The mechanism of this syndrome is not understood. Discontinue VOSTALLY if patient develops jaundice or marked elevations of hepatic enzymes.

5.5 Worsening Renal Function

Worsening renal function can be caused by ACE inhibitors, including VOSTALLY, as a consequence of inhibiting the renin-angiotensin-aldosterone system in susceptible individuals. In patients whose renal function may depend on the activity of the renin-angiotensin-aldosterone system, (e.g., patients with renal artery stenosis, chronic kidney disease, severe congestive heart failure, or volume depletion), treatment with ACE inhibitors, including VOSTALLY, may be associated with oliguria or progressive azotemia and rarely with acute renal failure or death. In such patients, monitor renal function during the first few weeks of therapy. Consider dose reduction, withholding, or discontinuing VOSTALLY in patients who develop a clinically significant decrease in renal function.

5.6 Hyperkalemia

Drugs that inhibit the renin angiotensin system, including VOSTALLY, can cause hyperkalemia. In clinical trials with ramipril, hyperkalemia (serum potassium >5.7 mEq/L) occurred in approximately 1% of hypertensive patients receiving ramipril. Risk factors for the development of hyperkalemia include renal insufficiency, diabetes mellitus, and the concomitant use of other drugs that raise serum potassium levels. Monitor serum potassium periodically in patients treated with VOSTALLY [see Drug Interactions (7.2)].

6 ADVERSE REACTIONS

6.1 Clinical Trials Experience

Because clinical trials are conducted under widely varying conditions, the adverse reaction rates observed in the clinical trials of a drug cannot be directly compared to rates in the clinical trials of another drug and may not reflect the rates observed in practice.

Hypertension

Ramipril has been evaluated for safety in over 4000 patients with hypertension; of these, 1230 patients were studied in U.S. controlled trials, and 1107 were studied in foreign controlled trials. Almost 700 of these patients were treated for at least one year. The overall incidence of reported adverse events was similar in ramipril and placebo patients.

The most common reasons for discontinuation of ramipril were cough (1.0%), dizziness (0.5%), and impotence (0.4%). In a later 1-year study, increased cough was seen in almost 12% of ramipril patients, with about 4% of patients requiring discontinuation of treatment.

Reduction in the Risk of Myocardial Infarction, Stroke, and Death from Cardiovascular Causes

HOPE Study

Safety data in the Heart Outcomes Prevention Evaluation (HOPE) study were collected as reasons for discontinuation or temporary interruption of treatment. The incidence of cough was similar to that seen in the Acute Infarction Ramipril Efficacy (AIRE) trial. The rate of angioedema was the same as in previous clinical trials [see Warnings and Precautions (5.2)] .

Post-Myocardial Infarction Heart Failure

AIRE Study

In AIRE, the adverse reactions occurring more commonly in ramipril than placebo and in >5% of patients taking ramipril were hypotension (11%) and cough (8%). The follow-up time was between 6 and 46 months for this study.

Clinical Laboratory Test Findings

Creatinine and Blood Urea Nitrogen: Increases in creatinine levels occurred in 1.2% of patients receiving ramipril alone, and in 1.5% of patients receiving ramipril and a diuretic. Increases in blood urea nitrogen levels occurred in 0.5% of patients receiving ramipril alone and in 3% of patients receiving ramipril with a diuretic. None of these increases required discontinuation of treatment. Increases in these laboratory values are more likely to occur in patients with renal insufficiency or those pretreated with a diuretic and based on experience with other ACE inhibitors, would be expected to be especially likely in patients with renal artery stenosis [see Warnings and Precautions (5.5)] .

Hemoglobin and Hematocrit: Decreases in hemoglobin or hematocrit (a low value and a decrease of 5 g/dL or 5%, respectively) were rare, occurring in 0.4% of patients receiving ramipril alone and in 1.5% of patients receiving ramipril plus a diuretic. No US patients discontinued treatment because of decreases in hemoglobin or hematocrit.

6.2 Post-Marketing Experience

Other Adverse Reactions

Other adverse reactions reported in controlled clinical trials (in less than 1% of ramipril patients,) or rarer events seen in post-marketing experience, include the following (in some, a causal relationship to drug is uncertain):

Cardiovascular: palpitations

General disorders: edema, malaise, weight gain

Hematologic: bone marrow depression, agranulocytosis, neutropenia, pancytopenia, hemolytic anemia, and thrombocytopenia

Gastrointestinal: pancreatitis, abdominal pain, anorexia, constipation, dry mouth, dyspepsia, dysphagia, increased salivation, and taste disturbance

Immune system: eosinophilic pneumonitis, hypersensitivity reactions (manifested by urticaria, pruritus, or rash, with or without fever), toxic epidermal necrolysis, Stevens-Johnson syndrome, an immune symptom complex which may include a positive ANA, an elevated erythrocyte sedimentation rate, arthralgia/arthritis, myalgia, fever, vasculitis, eosinophilia, photosensitivity, rash and other dermatologic manifestations

Musculoskeletal and connective tissue: arthralgia, arthritis, myalgia

Neurologic and Psychiatric: anxiety, amnesia, convulsions, depression, hearing loss, insomnia, nervousness, neuralgia, neuropathy, paresthesia, somnolence, tinnitus, tremor, vertigo, and vision disturbances

Respiratory, thoracic and mediastinal: dyspnea, epistaxis

Reproductive system: impotence

Skin and subcutaneous tissue: erythema multiforme, hyperhidrosis, photosensitivity, purpura, onycholysis, pemphigus, pemphigoid

In addition to adverse reactions reported from clinical trials, there have been rare reports of hypoglycemia reported during ramipril therapy when given to patients concomitantly taking oral hypoglycemic agents or insulin. The causal relationship is unknown.

7 DRUG INTERACTIONS

7.1 Diuretics

Patients on diuretics, especially those in whom diuretic therapy was recently instituted, may occasionally experience an excessive reduction of blood pressure after initiation of therapy with VOSTALLY. The possibility of hypotensive effects with VOSTALLY can be minimized by either decreasing or discontinuing the diuretic or increasing the salt intake prior to initiation of treatment with VOSTALLY. If this is not possible, reduce the starting dose [see Dosage and Administration (2)].

7.2 Agents Increasing Serum Potassium

Coadministration of VOSTALLY with other drugs that raise serum potassium levels may result in hyperkalemia. Monitor serum potassium in such patients.

7.3 Dual Blockade of the Renin-Angiotensin-Aldosterone System

Dual blockade of the RAS with angiotensin receptor blockers, ACE inhibitors, or aliskiren is associated with increased risks of hypotension, hyperkalemia, and changes in renal function (including acute renal failure) compared to monotherapy. In general, avoid combined use of RAS inhibitors. Closely monitor blood pressure, renal function and electrolytes in patients on VOSTALLY and other agents that affect the RAS.

Telmisartan

The ONTARGET trial enrolled 25,620 patients >55 years old with atherosclerotic disease or diabetes with end-organ damage, randomized them to telmisartan only, ramipril only, or the combination, and followed them for a median of 56 months. Patients receiving the combination of telmisartan and ramipril did not obtain any benefit in the composite endpoint of cardiovascular death, MI, stroke and heart failure hospitalization compared to monotherapy, but experienced an increased incidence of clinically important renal dysfunction (death, doubling of serum creatinine, or dialysis) compared with groups receiving telmisartan alone or ramipril alone. Concomitant use of telmisartan and ramipril (including VOSTALLY) is not recommended.

Aliskiren

Do not co-administer aliskiren with VOSTALLY in patients with diabetes. Avoid concomitant use of aliskiren with VOSTALLY in patients with renal impairment (GFR <60 mL/min/1.73 m^2).

7.4 Lithium

Increased serum lithium levels and symptoms of lithium toxicity have been reported in patients receiving ACE inhibitors during therapy with lithium; therefore, frequent monitoring of serum lithium levels is recommended. If a diuretic is also used, the risk of lithium toxicity may be increased.

7.5 Gold

Nitritoid reactions (symptoms include facial flushing, nausea, vomiting and hypotension) have been reported rarely in patients on therapy with injectable gold (sodium aurothiomalate) and concomitant ACE inhibitor therapy including VOSTALLY.

7.6 Non-Steroidal Anti-Inflammatory Agents including Selective Cyclooxygenase-2 Inhibitors (COX-2 Inhibitors)

In patients who are elderly, volume-depleted (including those on diuretic therapy), or with compromised renal function, co-administration of NSAIDs, including selective COX-2 inhibitors, with ACE inhibitors, including ramipril, may result in deterioration of renal function, including possible acute renal failure. These effects are usually reversible. Monitor renal function periodically in patients receiving ramipril and NSAID therapy.

The antihypertensive effect of ACE inhibitors, including ramipril, may be attenuated by NSAIDs.

7.7 mTOR Inhibitors or Other Drugs Known to Cause Angioedema

Patients taking concomitant mTOR inhibitor (e.g. temsirolimus) therapy or a neprilysin inhibitor may be at increased risk for angioedema. [see Warnings and Precautions (5.2)]

8 USE IN SPECIFIC POPULATIONS

8.1 Pregnancy

Risk Summary

VOSTALLY can cause fetal harm when administered to a pregnant woman. Use of drugs that act on the renin-angiotensin system during the second and third trimesters of pregnancy reduces fetal renal function and increases fetal and neonatal morbidity and death. Most epidemiologic studies examining fetal abnormalities after exposure to antihypertensive use in the first trimester have not distinguished drugs affecting the renin-angiotensin system from other antihypertensive agents. When pregnancy is detected, discontinue VOSTALLY as soon as possible.

The background risk of major birth defects and miscarriage for the indicated population is unknown. In the general U.S. population, the estimated background risk of major birth defects and miscarriage in clinically recognized pregnancies is 2-4% and 15-20% respectively.

Clinical Considerations

Disease-associated Maternal and/or Embryo/Fetal Risk

Hypertension in pregnancy increases the maternal risk for pre-eclampsia, gestational diabetes, premature delivery, and delivery complications (e.g., need for cesarean section, and post-partum hemorrhage). Hypertension increases the fetal risk for intrauterine growth restriction and intrauterine death. Pregnant women with hypertension should be carefully monitored and managed accordingly.

Fetal/Neonatal Adverse Reactions

Oligohydramnios in pregnant women who use drugs affecting the renin-angiotensin system in the second and third trimesters of pregnancy can result in the following: reduced fetal renal function leading to anuria and renal failure, fetal lung hypoplasia and skeletal deformations, including skull hypoplasia, hypotension, and death. In the unusual case that there is no appropriate alternative to therapy with drugs affecting the renin-angiotensin system for a particular patient, apprise the mother of the potential risk to the fetus.

Perform serial ultrasound examinations to assess the intra-amniotic environment. Fetal testing may be appropriate, based on the week of pregnancy. Patients and physicians should be aware, however, that oligohydramnios may not appear until after the fetus has sustained irreversible injury. Closely observe infants with histories of in utero exposure to VOSTALLY for hypotension, oliguria, and hyperkalemia. If oliguria or hypotension occur in neonates with a history of in utero exposure to VOSTALLY, support blood pressure and renal perfusion. Exchange transfusions or dialysis may be required as a means of reversing hypotension and substituting for disordered renal function.

8.2 Lactation

Risk Summary

Ingestion of a single 10 mg oral dose of ramipril resulted in undetectable amounts of ramipril and its metabolites in breast milk. However, multiple doses may produce low milk concentrations that are not predictable from a single dose. There are no available data on the effects of ramipril and its metabolites on the breastfed infant or on milk production. Because of the potential for severe adverse reactions in the breastfed infant, including hypotension, hyperkalemia and renal impairment, advise women not to breastfeed during treatment with VOSTALLY.

8.4 Pediatric Use

Safety and effectiveness in pediatric patients have not been established. Irreversible kidney damage has been observed in very young rats given a single dose of ramipril. Use of VOSTALLY is not recommended in children less than 2 years of age. It is not known whether post-natal use of ramipril, before maturation of renal function is complete, has a long-term deleterious effect on the kidney.

Neonates with a history of in utero exposure to ramipril:

If oliguria or hypotension occurs, direct attention toward support of blood pressure and renal perfusion. Exchange transfusions or dialysis may be required as a means of reversing hypotension and/or substituting for disordered renal function.

8.5 Geriatric Use

Of the total number of patients who received ramipril in U.S. clinical studies of ramipril, 11.0% were ≥65 years of age while 0.2% were ≥75 years of age. No overall differences in effectiveness or safety were observed between these patients and younger patients, and other reported clinical experience has not identified differences in responses between the elderly and younger patients, but a greater sensitivity of some older individuals cannot be ruled out.

One pharmacokinetic study conducted in hospitalized elderly patients indicated that peak ramiprilat levels and area under the plasma concentration-time curve (AUC) for ramiprilat are higher in older patients.

8.6 Renal Impairment

In patients of creatinine clearance 40-80 mL/min, 15-40 mL/min, and <15 mL/min, the exposure of ramiprilat was approximately 1.7-fold higher, 3.0-fold higher, and 3.2-fold higher respectively, compared to the group with Creatinine clearance >80mL/min. Overall, the results suggest that the starting dose of ramipril should be adjusted in patients with creatinine clearance <40 mL/min [see Dosage and Administration (2.5)].

8.7 Impaired Liver Function

As ramipril is primarily metabolized by hepatic esterases to its active moiety, ramiprilat, patients with impaired liver function could develop markedly elevated plasma levels of ramipril. No formal pharmacokinetic studies have been carried out in hypertensive patients with impaired liver function.

10 OVERDOSAGE

Single oral doses of ramipril in rats and mice of 10 g/kg–11 g/kg resulted in significant lethality. In dogs, oral doses as high as 1 g/kg induced only mild gastrointestinal distress. Limited data on human overdosage are available. The most likely clinical manifestations would be symptoms attributable to hypotension.

Laboratory determinations of serum levels of ramipril and its metabolites are not widely available, and such determinations have, in any event, no established role in the management of ramipril overdose.

No data are available to suggest physiological maneuvers (e.g., maneuvers to change the pH of the urine) that might accelerate elimination of ramipril and its metabolites. Similarly, it is not known which, if any, of these substances can be effectively removed from the body by hemodialysis.

Angiotensin II could presumably serve as a specific antagonist-antidote in the setting of ramipril overdose, but angiotensin II is essentially unavailable outside of scattered research facilities. Because the hypotensive effect of ramipril is achieved through vasodilation and effective hypovolemia, it is reasonable to treat ramipril overdose by infusion of normal saline solution.

11 DESCRIPTION

Ramipril is an angiotensin converting enzyme (ACE) inhibitor. It is a white, crystalline substance soluble in polar organic solvents and buffered aqueous solutions. Ramipril melts between 105°C–112°C.

Ramipril’s chemical name is (2S,3aS,6aS)-1[(S)-N-[(S)-1-Carboxy-3- phenylpropyl] alanyl] octahydrocyclopenta [b]pyrrole-2-carboxylic acid, 1-ethyl ester.

The structural formula for ramipril is:

Its empirical formula is C23H32N2O5and its molecular weight is 416.5 g/mol.

VOSTALLY is a clear, colorless solution for oral use that contains 1 mg/mL ramipril. The inactive ingredients are citric acid monohydrate, ethylparaben sodium, frozen peppermint flavor 5015241T, methylparaben sodium, purified water, and sucralose.

12 CLINICAL PHARMACOLOGY

12.1 Mechanism of Action

Ramipril and ramiprilat inhibit ACE in human subjects and animals. Angiotensin converting enzyme is a peptidyl dipeptidase that catalyzes the conversion of angiotensin I to the vasoconstrictor substance, angiotensin II. Angiotensin II also stimulates aldosterone secretion by the adrenal cortex. Inhibition of ACE results in decreased plasma angiotensin II, which leads to decreased vasopressor activity and to decreased aldosterone secretion. The latter decrease may result in a small increase of serum potassium. In hypertensive patients with normal renal function treated with ramipril alone for up to 56 weeks, approximately 4% of patients during the trial had an abnormally high serum potassium and an increase from baseline greater than 0.75 mEq/L, and none of the patients had an abnormally low potassium and a decrease from baseline greater than 0.75 mEq/L. In the same study, approximately 2% of patients treated with ramipril and hydrochlorothiazide for up to 56 weeks had abnormally high potassium values and an increase from baseline of 0.75 mEq/L or greater; and approximately 2% had abnormally low values and decreases from baseline of 0.75 mEq/L or greater [see Warnings and Precautions (5.8)] . Removal of angiotensin II negative feedback on renin secretion leads to increased plasma renin activity.

The effect of ramipril on hypertension appears to result at least in part from inhibition of both tissue and circulating ACE activity, thereby reducing angiotensin II formation in tissue and plasma.

Angiotensin converting enzyme is identical to kininase, an enzyme that degrades bradykinin. Whether increased levels of bradykinin, a potent vasopressor peptide, play a role in the therapeutic effects of VOSTALLY remains to be elucidated.

While the mechanism through which VOSTALLY lowers blood pressure is believed to be primarily suppression of the renin- angiotensin-aldosterone system, VOSTALLY has an antihypertensive effect even in patients with low-renin hypertension.

Although VOSTALLY was antihypertensive in all races studied, Black hypertensive patients (usually a low-renin hypertensive population) had a blood pressure lowering response to monotherapy, albeit a smaller average response, than non-Black patients.

12.2 Pharmacodynamics

Single doses of ramipril of 2.5 mg–20 mg produce approximately 60%–80% inhibition of ACE activity 4 hours after dosing with approximately 40%–60% inhibition after 24 hours. Multiple oral doses of ramipril of 2.5 mg or more cause plasma ACE activity to fall by more than 90% 4 hours after dosing, with over 80% inhibition of ACE activity remaining 24 hours after dosing. The more prolonged effect of even small multiple doses presumably reflects saturation of ACE binding sites by ramiprilat and relatively slow release from those sites.

12.3 Pharmacokinetics

Plasma concentrations of ramipril and ramiprilat (active metabolite) increase with increase in dose but are not strictly dose-proportional. The 24-hour AUC for ramiprilat, however, is dose-proportional over the 2.5 mg - 20 mg dose range. After once-daily dosing, steady-state plasma concentrations of ramiprilat are reached by the fourth dose. Steady-state concentrations of ramiprilat are somewhat higher than those seen after the first dose of ramipril, especially at low doses (2.5 mg), but the difference is not clinically significant plasma concentrations of ramiprilat decline in a triphasic manner (initial rapid decline, apparent elimination phase, terminal elimination phase).

Absorption

Following oral administration of VOSTALLY, peak plasma concentrations (Cmax) of ramipril are reached within 1 hour. Peak plasma concentrations of ramiprilat are reached 1–6 hours after drug intake. The absolute bioavailability of ramipril and ramiprilat were 28% and 44%, respectively, when 5 mg of oral ramipril was compared with the same dose of ramipril given intravenously.

Effect of food

The extent of absorption is not significantly influenced by the presence of food in the gastrointestinal tract, although the rate of absorption is reduced.

Distribution

The serum protein binding is about 73% for ramipril and about 56% for ramiprilat; in vitro, these percentages are independent of concentration over the range of 0.01 μg/mL–10 μg/mL The initial rapid decline, which represents distribution of the drug into a large peripheral compartment and subsequent binding to both plasma and tissue ACE, has a half-life of 2–4 hours.

Elimination

Because of its potent binding to ACE and slow dissociation from the enzyme, ramiprilat shows two elimination phases. The apparent elimination phase corresponds to the clearance of free ramiprilat and has a half-life of 9–18 hours. The terminal elimination phase has a prolonged half-life (>50 hours) and probably represents the binding/dissociation kinetics of the ramiprilat/ACE complex. It does not contribute to the accumulation of the drug. After multiple daily doses of ramipril 5 mg - 10 mg, the half-life of ramiprilat concentrations within the therapeutic range was 13–17 hours.

Metabolism

Cleavage of the ester group (primarily in the liver) converts ramipril to its active diacid metabolite, ramiprilat. Ramipril is almost completely metabolized to ramiprilat, which has about 6 times the ACE inhibitory activity of ramipril, and to the diketopiperazine ester, the diketopiperazine acid, and the glucuronides of ramipril and ramiprilat, all of which are inactive.

Excretion

After oral administration of ramipril, about 60% of the parent drug and its metabolites are eliminated in the urine, and about 40% is found in the feces. Drug recovered in the feces may represent both biliary excretion of metabolites and/or unabsorbed drug, however the proportion of a dose eliminated by the bile has not been determined. Less than 2% of the administered dose is recovered in urine as unchanged ramipril.

Specificpopulations

Patient with Renal Impairment

The urinary excretion of ramipril, ramiprilat, and their metabolites is reduced in patients with impaired renal function. Compared to normal subjects, patients with creatinine clearance <40 mL/min/1.73 m^2had higher peak and trough ramiprilat levels and slightly longer times to peak concentrations. In patients with creatinine clearance <40 mL/min/1.73 m^2, peak levels of ramiprilat are approximately doubled, and trough levels may be as much as quintupled. In multiple-dose regimens, the total exposure to ramiprilat (AUC) in these patients is 3–4 times greater than in patients with normal renal function who receive similar doses.

Patient with Hepatic Impairment

In patients with impaired liver function, the metabolism of ramipril to ramiprilat appears to be slowed, possibly because of diminished activity of hepatic esterases, and plasma ramipril levels in these patients are increased about 3-fold. Peak concentrations of ramiprilat in these patients, however, are not different from those seen in subjects with normal hepatic function, and the effect of a given dose on plasma ACE activity does not vary with hepatic function.

13 NONCLINICAL TOXICOLOGY

13.1 Carcinogenesis, Mutagenesis, Impairment of Fertility

No evidence of a tumorigenic effect was found when ramipril was given by gavage to rats for up to 24 months at doses of up to 500 mg/kg/day or to mice for up to 18 months at doses of up to 1000 mg/kg/day. (For either species, these doses are about 200 times the maximum recommended human dose when compared on the basis of body surface area.) No mutagenic activity was detected in the Ames test in bacteria, the micronucleus test in mice, unscheduled DNA synthesis in a human cell line, or a forward gene-mutation assay in a Chinese hamster ovary cell line. Several metabolites and degradation products of ramipril were also negative in the Ames test. A study in rats with dosages as great as 500 mg/kg/day did not produce adverse effects on fertility.

No teratogenic effects of ramipril were seen in studies of pregnant rats, rabbits, and cynomolgus monkeys. On a body surface area basis, the doses used were up to approximately 400 times (in rats and monkeys) and 2 times (in rabbits) the recommended human dose.

14 CLINICAL STUDIES

14.1 Hypertension

Ramipril has been compared with other ACE inhibitors, beta-blockers, and thiazide diuretics as monotherapy for hypertension. It was approximately as effective as other ACE inhibitors and as atenolol.

Administration of VOSTALLY to patients with mild to moderate hypertension results in a reduction of both supine and standing blood pressure to about the same extent with no compensatory tachycardia. Symptomatic postural hypotension is infrequent, although it can occur in patients who are salt- and/or volume-depleted [see Warnings and Precautions (5.5)]. Use of VOSTALLY in combination with thiazide diuretics gives a blood pressure lowering effect greater than that seen with either agent alone.

In single-dose studies, doses of 5 mg–20 mg of ramipril lowered blood pressure within 1–2 hours, with peak reductions achieved 3–6 hours after dosing. The antihypertensive effect of a single dose persisted for 24 hours. In longer term (4–12 weeks) controlled studies, once-daily doses of 2.5 mg–10 mg were similar in their effect, lowering supine or standing systolic and diastolic blood pressures 24 hours after dosing by about 6/4 mmHg more than placebo. In comparisons of peak vs. trough effect, the trough effect represented about 50-60% of the peak response. In a titration study comparing divided bid vs. qd treatment, the divided regimen was superior, indicating that for some patients, the antihypertensive effect with once-daily dosing is not adequately maintained.

In most trials, the antihypertensive effect of ramipril increased during the first several weeks of repeated measurements. The antihypertensive effect of ramipril has been shown to continue during long-term therapy for at least 2 years. Abrupt withdrawal of ramipril has not resulted in a rapid increase in blood pressure. In both Caucasians and Blacks, hydrochlorothiazide (25 or 50 mg) was significantly more effective than ramipril.

Ramipril was less effective in blacks than in Caucasians. The effectiveness of ramipril was not influenced by age, sex, or weight.

In a baseline-controlled study of 10 patients with mild essential hypertension, blood pressure reduction was accompanied by a 15% increase in renal blood flow. In healthy volunteers, glomerular filtration rate was unchanged.

14.2 Reduction in Risk of Myocardial Infarction, Stroke, and Death from Cardiovascular Causes

The HOPE study was a large, multicenter, randomized, double-blind, placebo-controlled, 2 x 2 factorial design study conducted in 9541 patients (4645 on ramipril) who were 55 years or older and considered at high risk of developing a major cardiovascular event because of a history of coronary artery disease, stroke, peripheral vascular disease, or diabetes that was accompanied by at least one other cardiovascular risk factor (hypertension, elevated total cholesterol levels, low HDL levels, cigarette smoking, or documented microalbuminuria). Patients were either normotensive or under treatment with other antihypertensive agents. Patients were excluded if they had clinical heart failure or were known to have a low ejection fraction (<0.40). This study was designed to examine the long-term (mean of 5 years) effects of ramipril (10 mg orally once daily) on the combined endpoint of myocardial infarction, stroke, or death from cardiovascular causes.

The HOPE study results showed that ramipril (10 mg/day) significantly reduced the rate of myocardial infarction, stroke, or death from cardiovascular causes (826/4652 vs. 651/4645, relative risk 0.78), as well as the rates of the 3 components of the combined endpoint. The relative risk of the composite outcomes in the ramipril group as compared to the placebo group was 0.78% (95% confidence interval, 0.70–0.86). The effect was evident after about 1 year of treatment.

Table 1. Summary of Combined Components and Endpoints—HOPE Study
Outcome | Placebo (N=4652) n (%) | (ramipril) (N=4645) n (%) | Relative Risk (95% CI) P-Value
Combined Endpoint
Myocardial infarction, stroke, or death from cardiovascular cause | 826 (17.8%) | 651 (14.0%) | 0.78 (0.70–0.86) P=0.0001
Component Endpoint
Death from cardiovascular causes | 377 (8.1%) | 282 (6.1%) | 0.74 (0.64–0.87) P=0.0002
Myocardial infarction | 570 (12.3%) | 459 (9.9%) | 0.80 (0.70–0.90) P=0.0003
Stroke | 226 (4.9%) | 156 (3.4%) | 0.68 (0.56–0.84) P=0.0002
Overall Mortality
Death from any cause | 569 (12.2%) | 482 (10.4%) | 0.84 (0.75–0.95) P=0.005

Figure 1. Kaplan-Meier Estimates of the Composite Outcome of Myocardial Infarction, Stroke, or Death from Cardiovascular Causes in the Ramipril Group and the Placebo Group

Ramipril was effective in different demographic subgroups (i.e., gender, age), subgroups defined by underlying disease (e.g., cardiovascular disease, hypertension), and subgroups defined by concomitant medication. There were insufficient data to determine whether or not ramipril was equally effective in ethnic subgroups.

This study was designed with a prespecified substudy in diabetics with at least one other cardiovascular risk factor. Effects of ramipril on the combined endpoint and its components were similar in diabetics (N=3577) to those in the overall study population.

Table 2. Summary of Combined Endpoints and Components in Diabetics—HOPE Study
Outcome | Placebo (N=1769) n (%) | (ramipril) (N=1808) n (%) | Relative Risk Reduction (95% CI) P-Value
Combined Endpoint
Myocardial infarction, stroke, or death from cardiovascular cause | 351 (19.8%) | 277 (15.3%) | 0.25 (0.12–0.36) P=0.0004
Component Endpoint
Death from cardiovascular causes | 172 (9.7%) | 112 (6.2%) | 0.37 (0.21–0.51) P=0.0001
Myocardial infarction | 229 (12.9%) | 185 (10.2%) | 0.22 (0.06–0.36) P=0.01
Stroke | 108 (6.1%) | 76 (4.2%) | 0.33 (0.10–0.50) P=0.007

Figure 2. The Beneficial Effect of Treatment with ramipril on the Composite Outcome of Myocardial Infarction, Stroke, or Death from Cardiovascular Causes Overall and in Various Subgroups

Cerebrovascular disease was defined as stroke or transient ischemic attacks. The size of each symbol is proportional to the number of patients in each group. The dashed line indicates overall relative risk.

The benefits of ramipril were observed among patients who were taking aspirin or other anti-platelet agents, beta- blockers, and lipid-lowering agents as well as diuretics and calcium channel blockers.

14.3 Post-Myocardial Infarction Heart Failure

Ramipril was studied in the AIRE trial. This was a multinational (mainly European) 161-center, 2006-patient, double- blind, randomized, parallel-group study comparing ramipril to placebo in stable patients, 2–9 days after an acute myocardial infarction, who had shown clinical signs of congestive heart failure at any time after the myocardial infarction. Patients in severe (NYHA class IV) heart failure, patients with unstable angina, patients with heart failure of congenital or valvular etiology, and patients with contraindications to ACE inhibitors were all excluded. The majority of patients had received thrombolytic therapy at the time of the index infarction, and the average time between infarction and initiation of treatment was 5 days.

Patients randomized to ramipril treatment were given an initial dose of 2.5 mg twice daily. If the initial regimen caused undue hypotension, the dose was reduced to 1.25 mg, but in either event doses were titrated upward (as tolerated) to a target regimen (achieved in 77% of patients randomized to ramipril) of 5 mg twice daily. Patients were then followed for an average of 15 months, with the range of follow-up between 6 and 46 months.

The use of ramipril was associated with a 27% reduction (p=0.002) in the risk of death from any cause; about 90% of the deaths that occurred were cardiovascular, mainly sudden death. The risks of progression to severe heart failure and of congestive heart failure-related hospitalization were also reduced, by 23% (p=0.017) and 26% (p=0.011), respectively.

The benefits of ramipril therapy were seen in both genders, and they were not affected by the exact timing of the initiation of therapy, but older patients may have had a greater benefit than those under 65. The benefits were seen in patients on (and not on) various concomitant medications. At the time of randomization these included aspirin (about 80% of patients), diuretics (about 60%), organic nitrates (about 55%), beta-blockers (about 20%), calcium channel blockers (about 15%), and digoxin (about 12%).

16 HOW SUPPLIED/STORAGE AND HANDLING

VOSTALLY is a clear, colorless, solution that contains 150 mL of ramipril solution 1 mg/mL. It is supplied in a glass bottle with child-resistant cap (NDC 69528-303-05).

Storage and Handling

Store in a refrigerator 2°C to 8°C (36°F to 46°F).

Store and dispense in original packaging. After the bottle is opened, store it between 20°C to 25°C (68°F to 77°F) [ see USP Controlled Room Temperature] and use it within 60 days.

17 PATIENT COUNSELING INFORMATION

Pregnancy

Advise female patients of reproductive potential about the consequences of exposure to VOSTALLY during pregnancy. Discuss treatment options with women planning to become pregnant. Ask patients to report pregnancies to their physicians as soon as possible [see Use in Specific Populations (8.1)].

Angioedema

Angioedema, including laryngeal edema, can occur with treatment with ACE inhibitors, especially following the first dose. Advise patients to immediately report any signs or symptoms suggesting angioedema (swelling of face, eyes, lips, or tongue, or difficulty in breathing) and to temporarily discontinue drug until they have consulted with the prescribing physician [see Warnings and Precautions (5.2)].

Symptomatic Hypotension

Inform patients that light-headedness can occur, especially during the first days of therapy, and it should be reported. Advise patients to discontinue VOSTALLY if syncope (fainting) occurs, and to follow up with their health care providers.

Inform patients that inadequate fluid intake or excessive perspiration, diarrhea, or vomiting while taking VOSTALLY can lead to an excessive fall in blood pressure, with the same consequences of lightheadedness and possible syncope [see Warnings and Precautions (5.3)].

Lactation

Advise women not to breastfeed during treatment with VOSTALLY [see Use in Specific Populations (8.2)].

Hyperkalemia

Advise patients not to use salt substitutes containing potassium without consulting their physician [see Warnings and Precautions (5.6)].

Hypoglycemia

Tell diabetic patients treated with oral antidiabetic agents or insulin starting an ACE inhibitor to monitor for hypoglycemia closely, especially during the first month of combined use [see Drug Interactions (7.2)].

Leukopenia/Neutropenia

Tell patients to report promptly any indication of infection (e.g., sore throat, fever), which may be a sign of leukopenia/neutropenia.

Administration Information

Instruct patients or caregivers to use an oral dosing syringe or oral dosing cup to correctly measure the prescribed amount of medication. Inform patients that oral dosing syringes may be obtained from their pharmacy.

Manufactured for:

Rosemont Pharmaceuticals LLC

Greenville, SC 29615

www.rosemontpharmaceuticals.com

VOSTALLY® is a registered trademark of Rosemont Pharmaceuticals Inc.

PI-RAM-01-001

PRINCIPAL DISPLAY PANEL - 150 mL Bottle

NDC 69528-303-05

VOSTALLY®
(ramipril)
Oral Solution

1 mg/mL

150mL